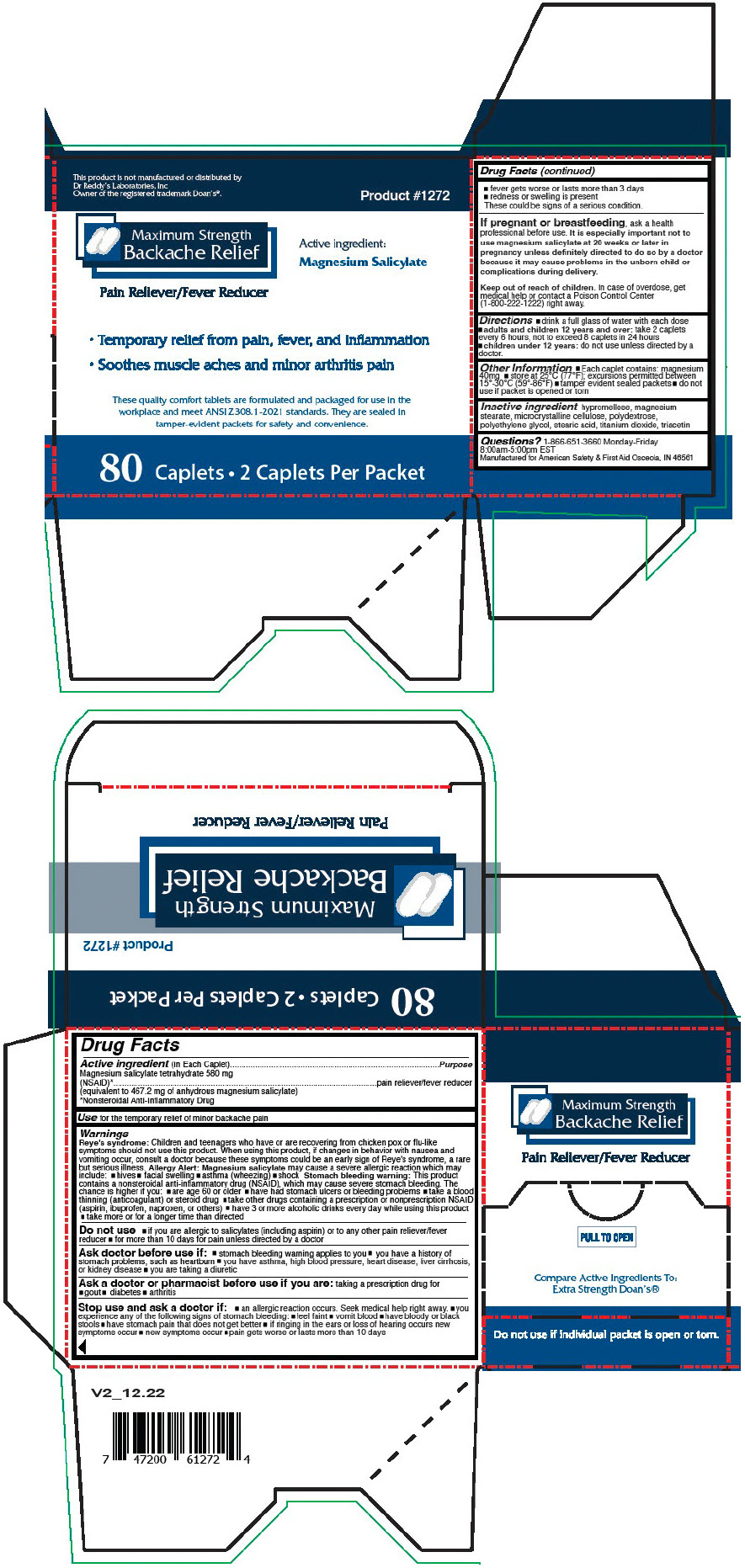 DRUG LABEL: Maximum Strength Backache Relief
NDC: 73598-1272 | Form: CAPSULE, COATED
Manufacturer: JHK DBA American Safety & First Aid
Category: otc | Type: HUMAN OTC DRUG LABEL
Date: 20241007

ACTIVE INGREDIENTS: MAGNESIUM SALICYLATE 580 mg/1 1
INACTIVE INGREDIENTS: HYPROMELLOSE, UNSPECIFIED; MAGNESIUM STEARATE; MICROCRYSTALLINE CELLULOSE; POLYDEXTROSE; POLYETHYLENE GLYCOL, UNSPECIFIED; STEARIC ACID; TITANIUM DIOXIDE; TRIACETIN

Maximum Strength Backache Relief

Drug Facts

Active ingredient (In Each Caplet)

Magnesium salicylate tetrahydrate 580 mg (NSAID) [Nonsteroidal Anti-Inflammatory Drug] (equivalent to 467.2 mg of anhydrous magnesium salicylate)

Purpose

pain reliever/fever reducer

Use

for the temporary relief of minor backache pain

Warnings

Reye's syndrome

Children and teenagers who have or are recovering from chicken pox or flu-like symptoms should not use this product. When using this product, if changes in behavior with nausea and vomiting occur, consult a doctor because these symptoms could be an early sign of Reye's syndrome, a rare but serious illness.

Allergy Alert

Magnesium salicylate may cause a severe allergic reaction which may include:

- hives
- facial swelling
- asthma (wheezing)
- shock

Stomach bleeding warning

This product contains a nonsteroidal anti-inflammatory drug (NSAID), which may cause severe stomach bleeding. The chance is higher if you:

- are age 60 or older
- have had stomach ulcers or bleeding problems
- take a blood thinning (anticoagulant) or steroid drug
- take other drugs containing a prescription or nonprescription NSAID (aspirin, ibuprofen, naproxen, or others)
- have 3 or more alcoholic drinks every day while using this product
- take more or for a longer time than directed

Do not use

- if you are allergic to salicylates (including aspirin) or to any other pain reliever/fever reducer
- for more than 10 days for pain unless directed by a doctor

Ask doctor before use if:

- stomach bleeding warning applies to you
- you have a history of stomach problems, such as heartburn
- you have asthma, high blood pressure, heart disease, liver cirrhosis, or kidney disease
- you are taking a diuretic

Ask a doctor or pharmacist before use if you are:

taking a prescription drug for

- gout
- diabetes
- arthritis

Stop use and ask a doctor if:

- an allergic reaction occurs. Seek medical help right away.
- you experience any of the following signs of stomach bleeding:
  - feel faint
  - vomit blood
  - have bloody or black stools
  - have stomach pain that does not get better
  - if ringing in the ears or loss of hearing occurs new symptoms occur
  - new symptoms occur
  - pain gets worse or lasts more than 10 days
  - fever gets worse or lasts more than 3 days
  - redness or swelling is present

These could be signs of a serious condition.

PREGNANCY OR BREAST FEEDING

If pregnant or breastfeeding, ask a health professional before use. It is especially important not to use magnesium salicylate at 20 weeks or later in pregnancy unless definitely directed to do so by a doctor because it may cause problems in the unborn child or complications during delivery.

Keep out of reach of children. In case of overdose, get medical help or contact a Poison Control Center (1-800-222-1222) right away.

Directions

- drink a full glass of water with each dose
- adults and children 12 years and over: take 2 caplets every 6 hours, not to exceed 8 caplets in 24 hours
- children under 12 years: do not use unless directed by a doctor.

Other Information

- Each caplet contains: magnesium 40mg
- store at 25°C (77°F); excursions permitted between 15°-30°C (59°-86°F)
- tamper evident sealed packets
- do not use if packet is opened or torn

Inactive ingredient

hypromellose, magnesium stearate, microcrystalline cellulose, polydextrose, polyethylene glycol, stearic acid, titanium dioxide, triacetin

Questions?

1-866-651-3660 Monday-Friday 8:00am-5:00pm EST

PRINCIPAL DISPLAY PANEL - 580 mg Caplet Packet Carton

This product is not manufactured or distributed by
Dr Reddy's Laboratories, Inc
Owner of the registered trademark Doan's®.

Maximum Strength
Backache Relief

Product #1272

Pain Reliever/Fever Reducer

Active ingredient:
Magnesium Salicylate

- Temporary relief from pain, fever, and inflammation
- Soothes muscle aches and minor arthritis pain

These quality comfort tablets are formulated and packaged for use in the
workplace and meet ANSI Z308.1-2021 standards. They are sealed in
tamper-evident packets for safety and convenience.

80 Caplets • 2 Caplets Per Packet